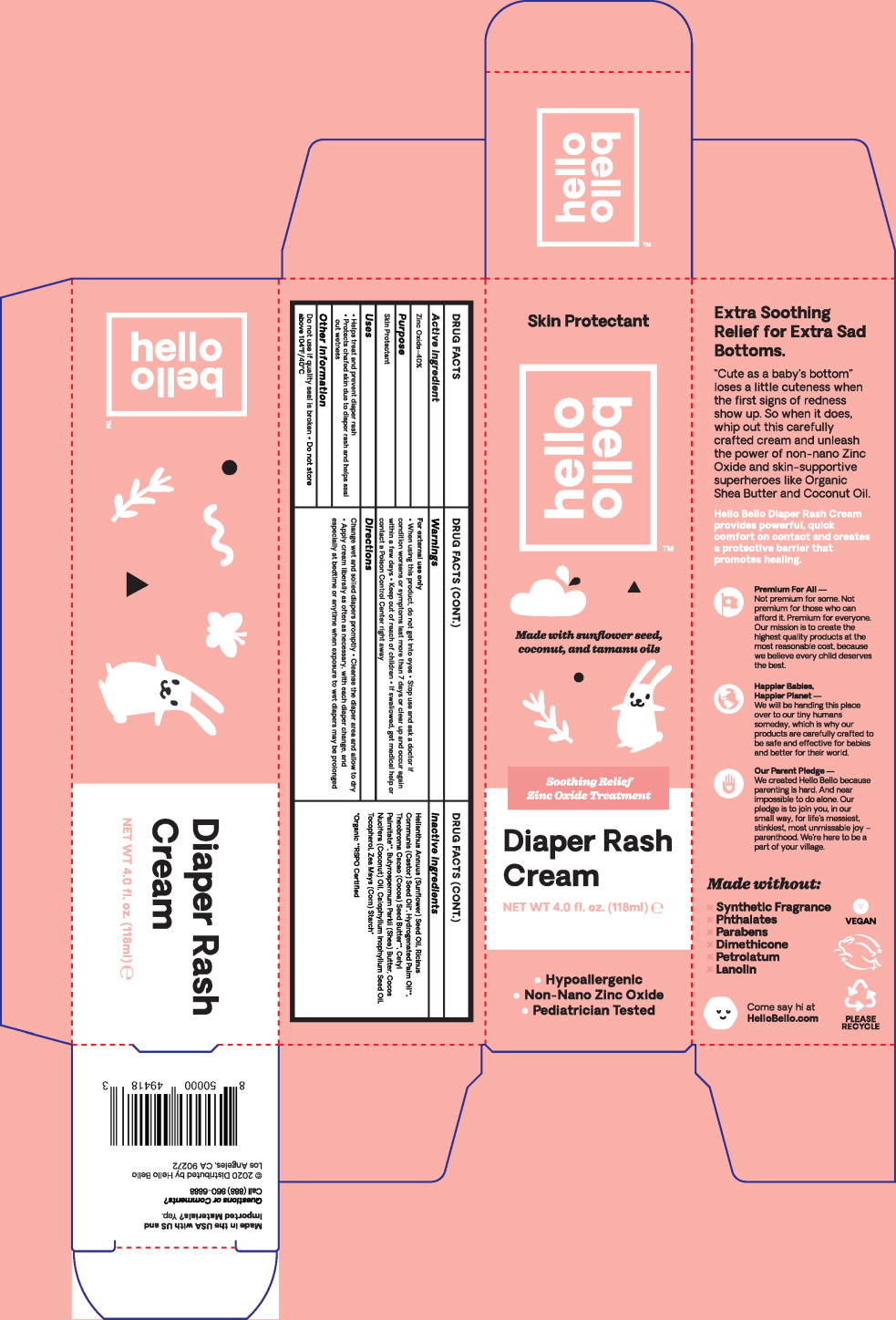 DRUG LABEL: Zinc Oxide
NDC: 73418-010 | Form: CREAM
Manufacturer: Unconditional Love d/b/a Hello Bello
Category: otc | Type: HUMAN OTC DRUG LABEL
Date: 20210108

ACTIVE INGREDIENTS: Zinc Oxide 480 g/1000 mL
INACTIVE INGREDIENTS: Sunflower Oil; Castor Oil; Hydrogenated Palm Oil; Cocoa butter; Cetyl Palmitate; Shea Butter; Coconut Oil; Tamanu oil; .Alpha.-Tocopherol Acetate; Starch, Corn

DRUG FACTS

Active ingredient

Zinc Oxide-40%

Purpose

Skin Protectant

Uses

- Helps treat and prevent diaper rash
- Protects chafed skin due to diaper rash and helps seal out wetness

Other information

Do not use if quality seal is broken

- Do not store above 104°F/40°C

Warnings

For external use only

- When using this product, do not get into eyes

- Stop use and ask a doctor if condition worsens or symptoms last more than 7 days or clear up and occur again within a few days

- Keep out of reach of children
- If swallowed, get medical help or contact a Poison Control Center right away

Directions

Change wet and soiled diapers promptly

- Cleanse the diaper area and allow to dry
- Apply cream liberally as often as necessary, with each diaper change, and especially at bedtime or anytime when exposure to wet diapers may be prolonged

INACTIVE INGREDIENT

Helianthus Annuus (Sunflower) Seed Oil, Ricinus Communis (Castor) Seed Oil*, Hydrogenated Palm Oil**, Theobroma Cacao (Cocoa) Seed Butter**, Cetyl Palmitate**, Butyrospermum Parkii (Shea) Butter, Cocos Nucifera (Coconut) Oil, Calophyllum Inophyllum Seed Oil, Tocopherol, Zea Mays (Corn) Starch*

*Organic **RSPO Certified

Principal Display Panel – 118 mL Carton Label

Skin Protectant

hello
bello™

Made with sunflower seed,
coconut, and tamanu oils

Soothing Relief
Zinc Oxide Treatment

Diaper Rash
Cream

NET WT 4.0 fl. oz. (118ml) e

- Hypoallergenic
- Non-Nano Zinc Oxide
- Pediatrician Tested